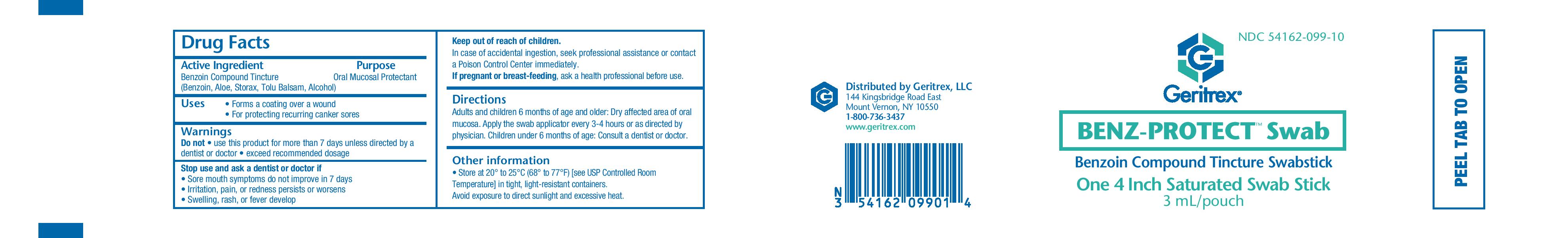 DRUG LABEL: Benz Protect
NDC: 54162-099 | Form: LIQUID
Manufacturer: Geritrex LLC
Category: otc | Type: HUMAN OTC DRUG LABEL
Date: 20171027

ACTIVE INGREDIENTS: BENZOIN RESIN 100 mg/1 mL
INACTIVE INGREDIENTS: ALCOHOL; ALOE; LIQUIDAMBAR ORIENTALIS RESIN; TOLU BALSAM

Benz Protect

Active Ingredient

Benzoin Compound Tincture (Benzoin, Aloe, Storax, Tolu, Balsam, Alcohol)

Intended Use

- Forms a coating over a wound
- For protecting recurring canker sores

Directions

For adults and supervised children 2 years and older:
Dry affected area of skin or oral mucosa. Apply with a cotton
swab or gauze every 3-4 hours or as directed by your physician.

Warnings

Do not

- Use this product for more than 7 days unless directed by a dentist or doctor
- Exceed recommended dosage

Stop use and ask a dentist or doctor if

- Sore mouth symptoms do not improve in 7 days
- Irritation, pain, or redness persists or worsens
- Swelling, rash, or fever develop

Directions

Adults and children 6 months or age and older: Dry affected area of oral mucosa. Apply the swab applicator every 3-4 hours or as directed by physician. Children under 6 months of age: Consult a dentist or Doctor

STORAGE AND HANDLING

Store at 20° to 25°C (68° to 77° F) [see USP Controlled Room Temperature] in tight, light-resistant containers. Avoid exposure
to direct sunlight or heat.

KEEP OUT OF REACH OF CHILDREN.

In case of accidental ingestions, seek professional assistance or contact a Poison Control Center immediately

PREGNANCY OR BREAST FEEDING

If pregnant or breast-feeding, ask a health professional before use.